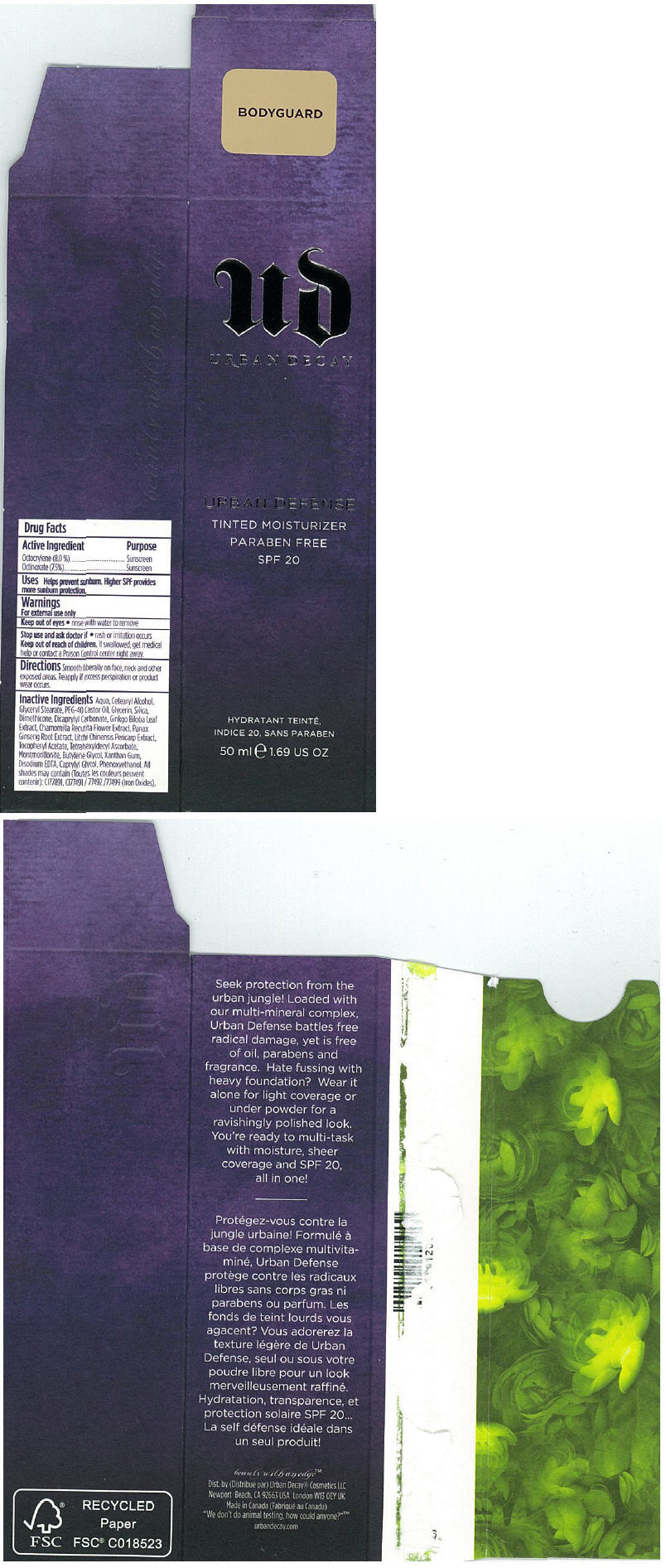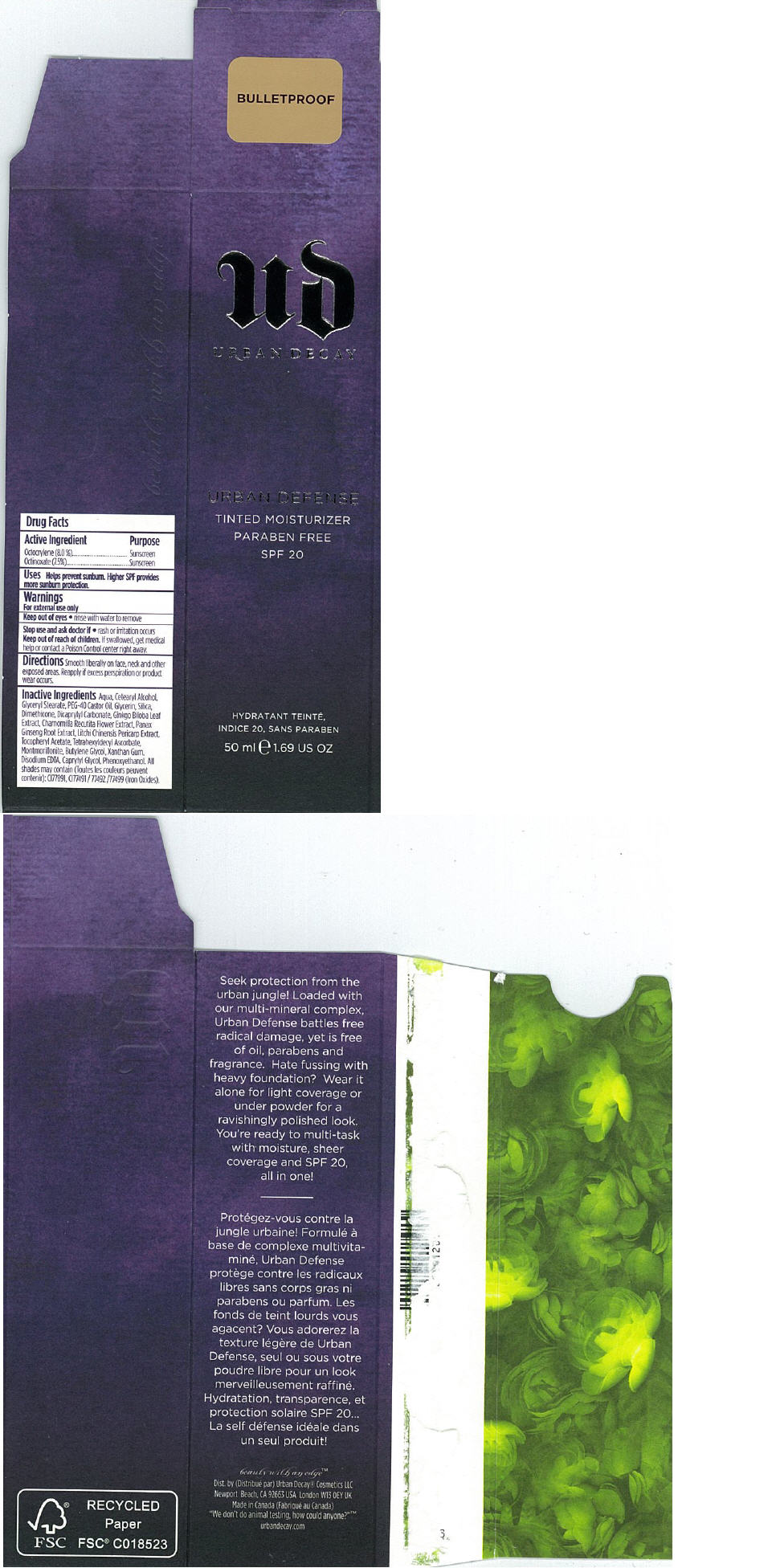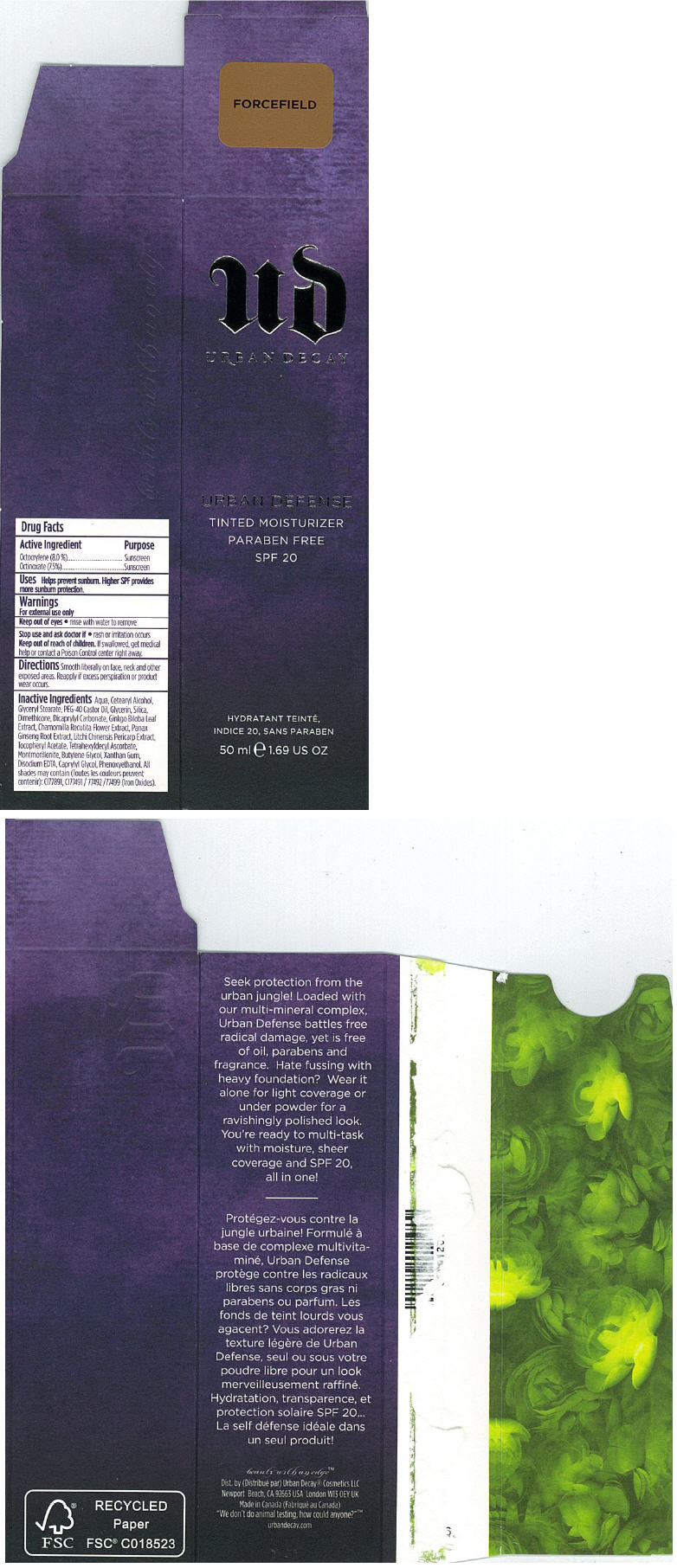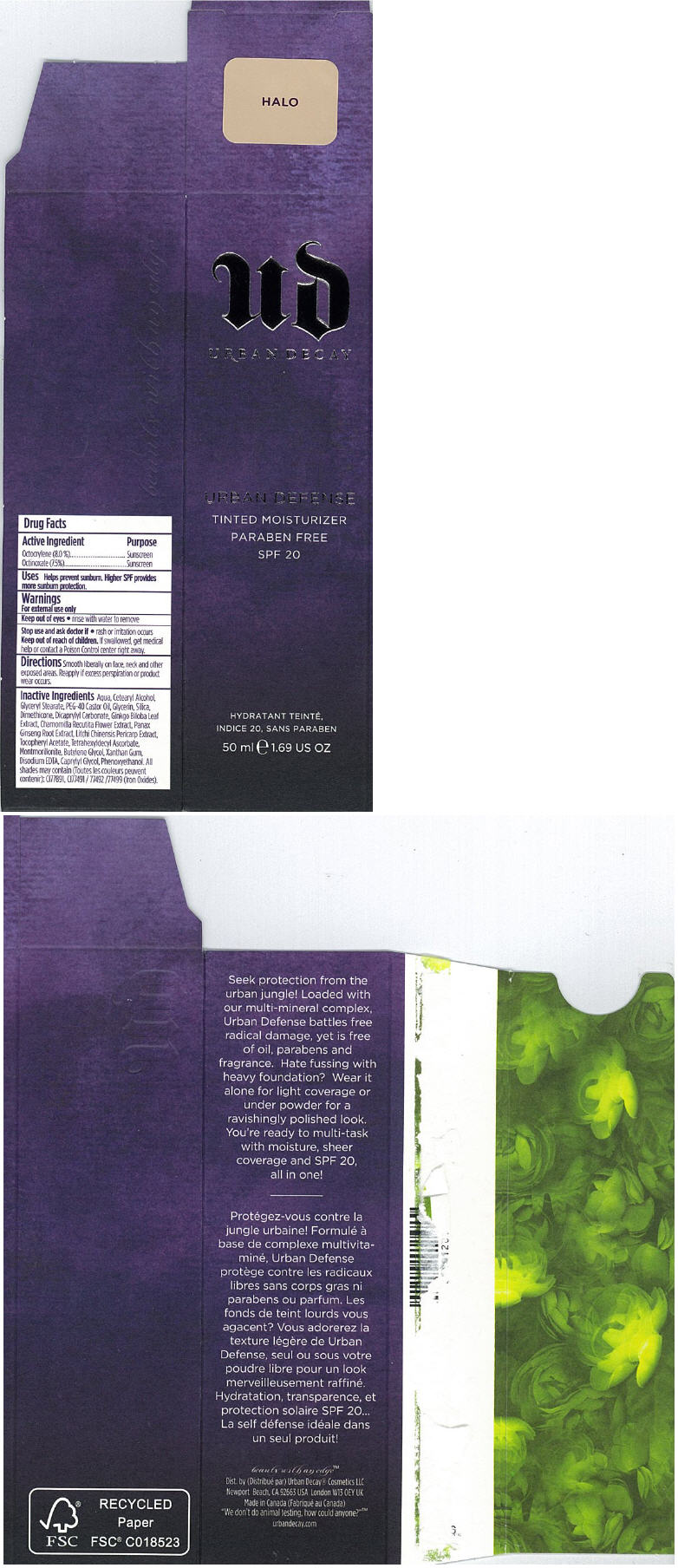 DRUG LABEL: Urban Defense
NDC: 51727-0631 | Form: EMULSION
Manufacturer: Urban Decay Cosmetics, LLC
Category: otc | Type: HUMAN OTC DRUG LABEL
Date: 20120702

ACTIVE INGREDIENTS: Octocrylene 4 mL/50 mL; Octinoxate 3.75 mL/50 mL
INACTIVE INGREDIENTS: WATER; CETOSTEARYL ALCOHOL; GLYCERYL MONOSTEARATE; POLYOXYL 40 CASTOR OIL; GLYCERIN; SILICON DIOXIDE; DIMETHICONE; DICAPRYLYL CARBONATE; GINKGO; MATRICARIA RECUTITA; ASIAN GINSENG; LITCHI FRUIT; ACETATE ION; TETRAHEXYLDECYL ASCORBATE; MONTMORILLONITE; BUTYLENE GLYCOL; XANTHAN GUM; EDETATE DISODIUM; CAPRYLYL GLYCOL; PHENOXYETHANOL; TITANIUM DIOXIDE; FERRIC OXIDE RED

ud
URBAN DECAY
URBAN DEFENSE

Drug Facts

ACTIVE INGREDIENT

Active Ingredient | Purpose
Octocrylene (8.0 %) | Sunscreen
Octinoxate (7.5%) | Sunscreen

Uses

Helps prevent sunburn. Higher SPF provides more sunburn protection.

Warnings

For external use only

Keep out of eyes

- rinse with water to remove

Stop use and ask doctor if

- rash or irritation occurs

Keep out of reach of children. If swallowed, get medical help or contact a Poison Control center right away.

Directions

Smooth liberally on face, neck and other exposed areas. Reapply if excess perspiration or product wear occurs.

Inactive Ingredients

Aqua, Cetearyl Alcohol, Glyceryl Stearate, PEG-40 Castor Oil, Glycerin, Silica, Dimethicone, Dicaprylyl Carbonate, Ginkgo Biloba Leaf Extract, Chamomilla Recutita Flower Extract, Panax Ginseng Root Extract, Litchi Chinensis Pericarp Extract, Tocopheryl Acetate, Tetrahexyldecyl Ascorbate, Montmorillonite, Butylene Glycol, Xanthan Gum, Disodium EDTA, Caprylyl Glycol, Phenoxyethanol. All shades may contain (Toutes les couleurs peuvent contenir): CI77891, CI77491 / 77492 /77499 (Iron Oxides).

PRINCIPAL DISPLAY PANEL - 50 ml BODYGUARD Carton

ud
URBAN DECAY

URBAN DEFENSE

TINTED MOISTURIZER
PARABEN FREE
SPF 20

50 ml e 1.69 US OZ

PRINCIPAL DISPLAY PANEL - 50 ml BULLETPROOF Carton

ud
URBAN DECAY

URBAN DEFENSE

TINTED MOISTURIZER
PARABEN FREE
SPF 20

50 ml e 1.69 US OZ

PRINCIPAL DISPLAY PANEL - 50 ml FORCEFIELD Carton

ud
URBAN DECAY

URBAN DEFENSE

TINTED MOISTURIZER
PARABEN FREE
SPF 20

50 ml e 1.69 US OZ

PRINCIPAL DISPLAY PANEL - 50 ml HALO Carton

ud
URBAN DECAY

URBAN DEFENSE

TINTED MOISTURIZER
PARABEN FREE
SPF 20

50 ml e 1.69 US OZ